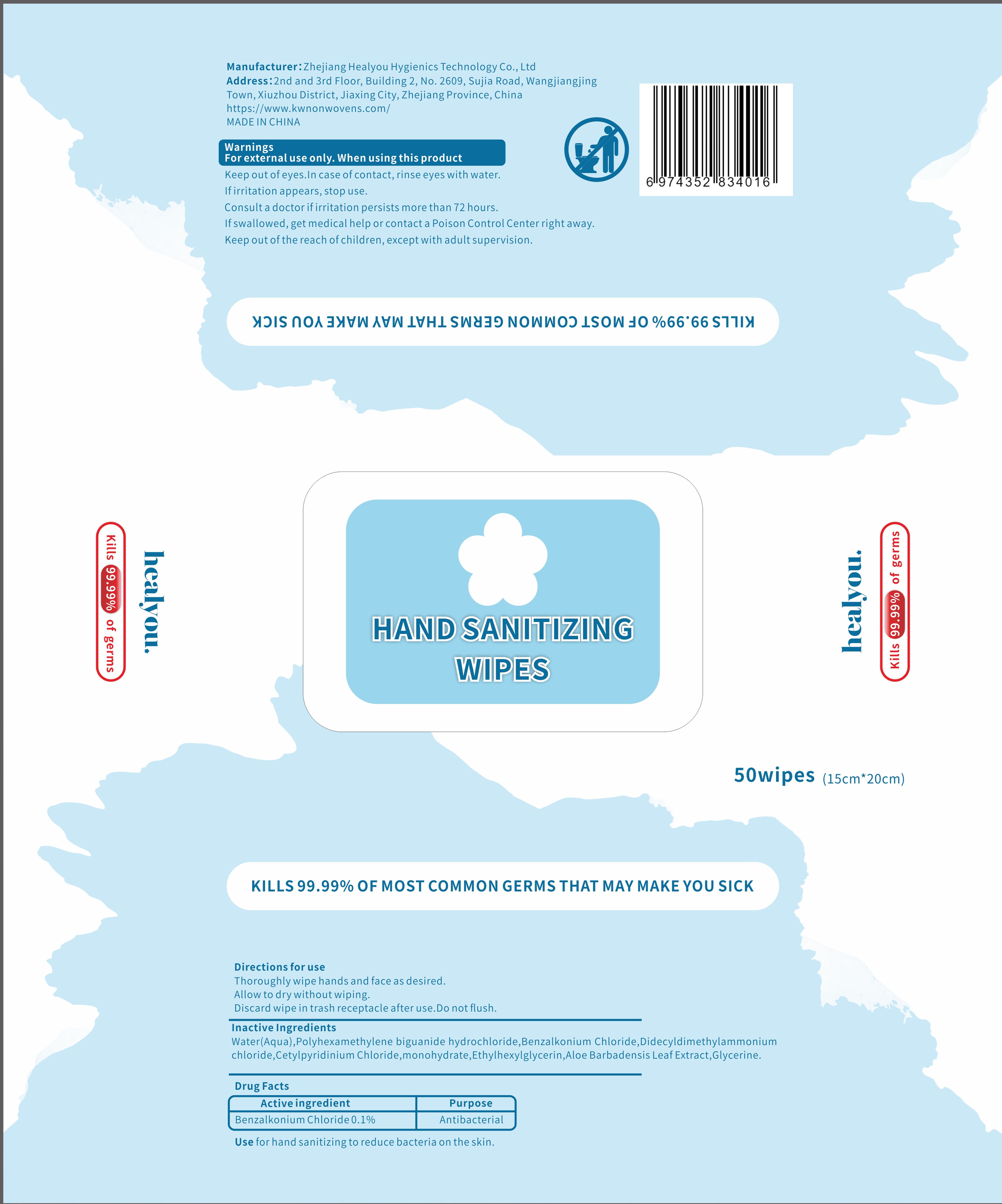 DRUG LABEL: HAND SANIT1ZING WIPES
NDC: 81925-001 | Form: CLOTH
Manufacturer: Zhejiang Healyou Hygienics Technology Co., Ltd.
Category: otc | Type: HUMAN OTC DRUG LABEL
Date: 20210517

ACTIVE INGREDIENTS: BENZALKONIUM CHLORIDE 0.001 mg/1 1
INACTIVE INGREDIENTS: WATER; POLIHEXANIDE HYDROCHLORIDE; DIDECYLDIMONIUM CHLORIDE; CETYLPYRIDINIUM CHLORIDE; ETHYLHEXYLGLYCERIN; GLYCERIN; ALOE VERA LEAF

ACTIVE INGREDIENT

Benzalkonium Chloride

PURPOSE

Antiseptic

Use

Use for hand sanitizing to reduce bacteria on the skin.

WARNINGS

For external use only.When using this product

lf irritation appears, stop use.

DO NOT USE

Keep out of eyes.In case of contact, rinse eyes with water.

ASK DOCTOR

Consult a doctor if irritation persists more than 72 hours.
lf swallowed,get medical help or contact a Poison Control Center right away.

KEEP OUT OF REACH OF CHILDREN

Keep out of the reach of children, except with adult supervision.

Directions

Thoroughly wipe hands and face as desired.
Allow to dry without wiping.
Discard wipe in trash receptacle after use.Do not flush.

INACTIVE INGREDIENT

Water(Aqua),Polyhexamethylene biguanide hydrochloride,Benzalkonium Chloride,Didecyldimethylammoniumchloride,Cetylpyridinium Chloride,monohydrate,Ethylhexylglycerin,Aloe Barbadensis Leaf Extract,Glycerine.

STORAGE AND HANDLING

Store at room temperature